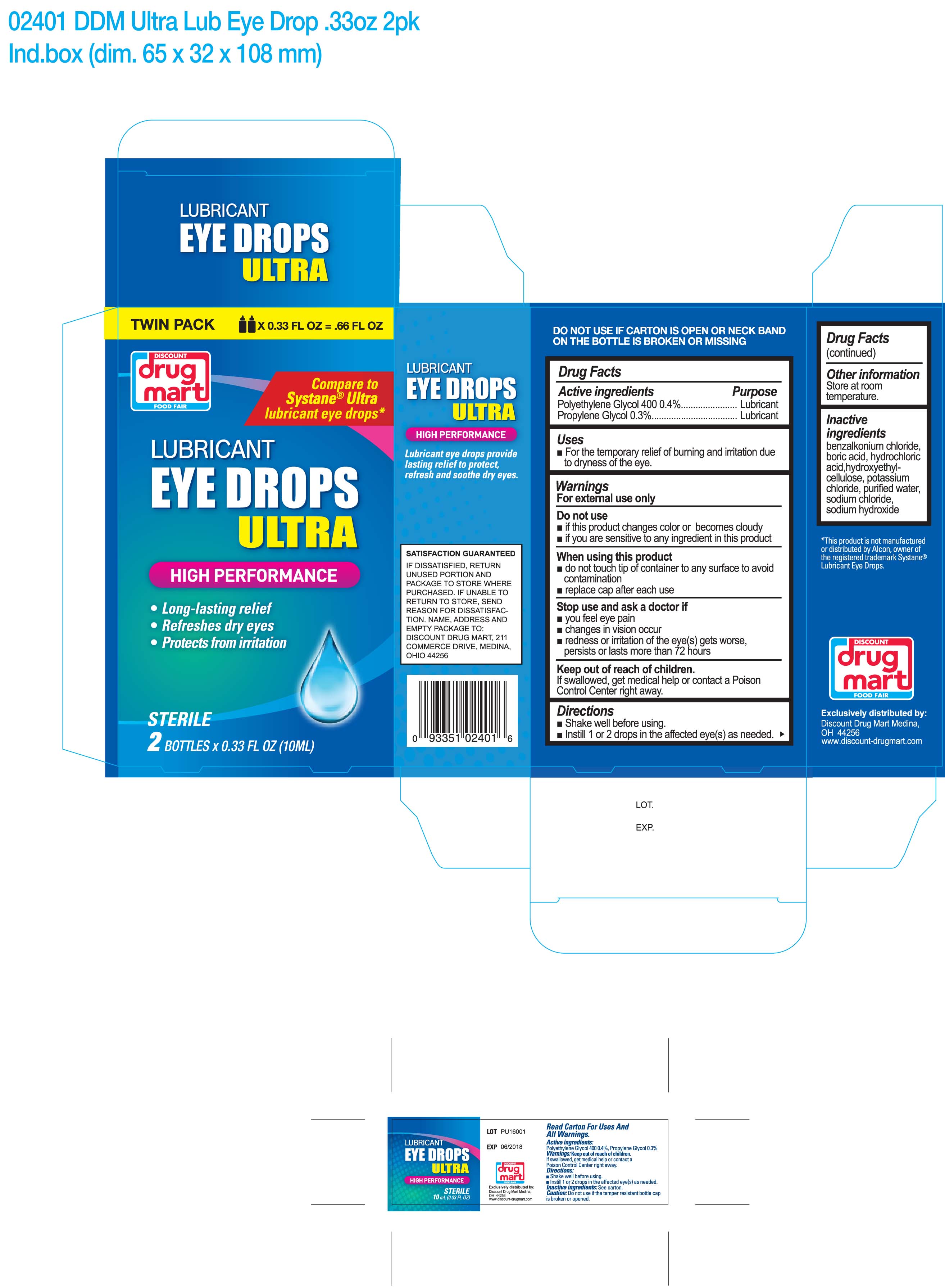 DRUG LABEL: Lubricant Eye Drops Ultra
NDC: 53943-240 | Form: LIQUID
Manufacturer: Discount Drug Mart
Category: otc | Type: HUMAN OTC DRUG LABEL
Date: 20170426

ACTIVE INGREDIENTS: POLYETHYLENE GLYCOL 400 4 mg/1 mL; PROPYLENE GLYCOL 3 mg/1 mL
INACTIVE INGREDIENTS: BENZALKONIUM CHLORIDE; BORIC ACID; HYDROCHLORIC ACID; POTASSIUM CHLORIDE; SODIUM CHLORIDE; SODIUM HYDROXIDE; WATER

Active ingredients

Polyethylene Glycol 400

Propylene Glycol

Purpose

Lubricant

Lubricant

Uses

- for the temporary relief of burning and irritation due to dryness of the eye

Warnings

For external use only

Do not use

- if this product changes color or becomes cloudy
- if you are sensitive to any ingredient in this product

When using this product

- do not touch tip of container to any surface to avoid contamination
- replace cap after each use

Stop use and ask a doctor if

- you feel eye pain
- changes in vision occur
- redness or irritation of the eye(s) gets worse, persists or lasts more than 72 hours

Keep out of reach of children.

If swallowed, get medical help or contact a Poison Control Center right away.

Directions

- Shake well before using
- Instill 1 or 2 drops in the affected eye(s) as needed.

Other information

Store at room temperature.

Inactive ingredients

benzalkonium chloride, boric acid, hydrochloric acid, hydroxyethyl cellulose, potassium chloride, purified water, sodium chloride, sodium hydroxide